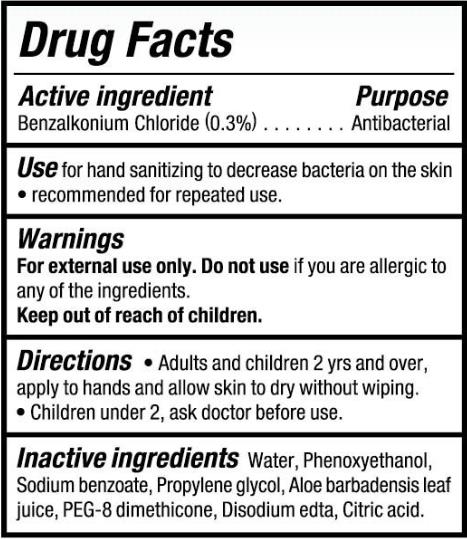 DRUG LABEL: WIPES
NDC: 77720-007 | Form: CLOTH
Manufacturer: Skaffles Group Limited Liability Company
Category: otc | Type: HUMAN OTC DRUG LABEL
Date: 20200723

ACTIVE INGREDIENTS: BENZALKONIUM CHLORIDE 0.3 g/100 g
INACTIVE INGREDIENTS: WATER; ALOE VERA LEAF; CITRIC ACID MONOHYDRATE; PEG-8 DIMETHICONE; DISODIUM EDTA-COPPER; PROPYLENE GLYCOL; PHENOXYETHANOL; SODIUM BENZOATE

77720-007 WIPES 0.3% BENZALKONIUM CHLORIDE

Active Ingredient

Benzalkonium Chloride 0.3%

Purpose

Antibacterial

USE

Use for hand sanitizing to decrease bacteria on the skin
recommended for repeated use.

Warning

For external use only. Do not use if you are allergic to
any of the ingredients.

Keep out of reach of children.

Directions

Directions● Adults and children 2 yrs and over,
apply to hands and allow skin to dry without wiping.
●Children under 2, ask doctor before use.

Inactive ingredients

Water, Phenoxyethanol,Sodium benzoate, Propylene glycol, Aloe barbadensis leaf juice, PEG-8 dimethicone, Disodium edta, Citric acid.